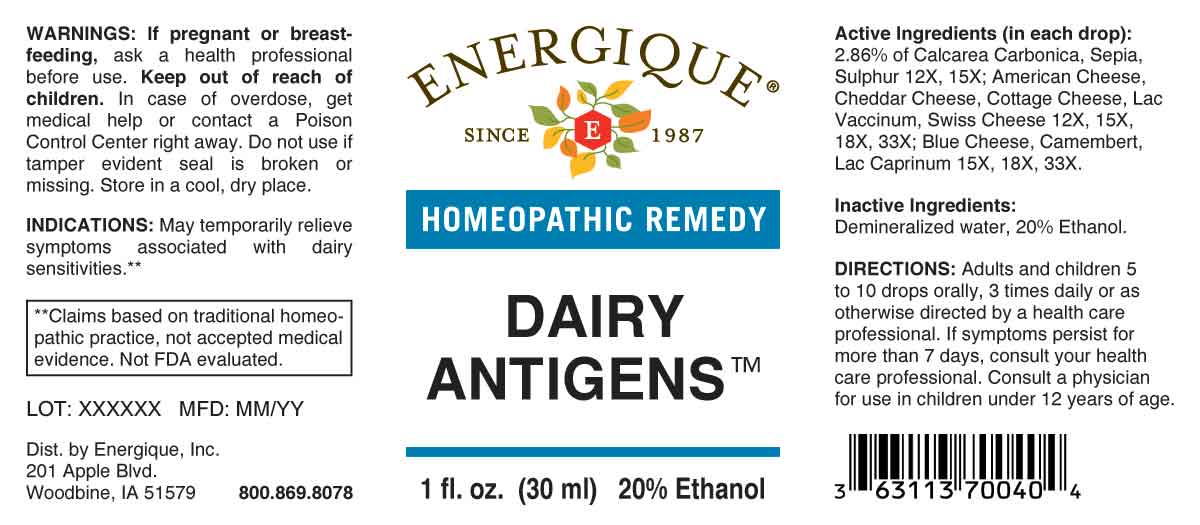 DRUG LABEL: Dairy Antigens
NDC: 44911-0687 | Form: LIQUID
Manufacturer: Energique, Inc.
Category: homeopathic | Type: HUMAN OTC DRUG LABEL
Date: 20231220

ACTIVE INGREDIENTS: OYSTER SHELL CALCIUM CARBONATE, CRUDE 12 [hp_X]/1 mL; SEPIA OFFICINALIS JUICE 12 [hp_X]/1 mL; SULFUR 12 [hp_X]/1 mL; WHEY 12 [hp_X]/1 mL; CASEIN, LACTOCOCCUS LACTIS CULTURED, PENICILLIUM ROQUEFORTI CULTURED, AGED 15 [hp_X]/1 mL; CASEIN, LACTOCOCCUS LACTIS CULTURED, PENICILLIUM CAMEMBERTI CULTURED, AGED 15 [hp_X]/1 mL; CASEIN, LACTOCOCCUS LACTIS CULTURED, AGED 12 [hp_X]/1 mL; CASEIN, LACTOCOCCUS LACTIS CULTURED 12 [hp_X]/1 mL; GOAT MILK 15 [hp_X]/1 mL; COW MILK 12 [hp_X]/1 mL; CASEIN, EMMENTAL CULTURED 12 [hp_X]/1 mL
INACTIVE INGREDIENTS: WATER; ALCOHOL

DRUG FACTS:

ACTIVE INGREDIENTS:

(in each drop): 2.86% of Calcarea Carbonica 12X, 15X, Sepia 12X, 15X, Sulphur 12X, 15X; American Cheese 12X, 15X, 18X, 33X, Cheddar Cheese 12X, 15X, 18X, 33X, Cottage Cheese 12X, 15X, 18X, 33X, Lac Vaccinum 12X, 15X, 18X, 33X, Swiss Cheese 12X, 15X, 18X, 33X; Blue Cheese 15X, 18X, 33X, Camembert 15X, 18X, 33X, Lac Caprinum 15X, 18X, 33X.

PURPOSE:

May temporarily relieve symptoms associated with dairy sensitivities.**

**Claims based on traditional homeopathic practice, not accepted medical evidence. Not FDA evaluated.

WARNINGS:

If pregnant or breast-feeding, ask a health professional before use.

Keep out of reach of children. In case of overdose, get medical help or contact a Poison Control Center right away.

Do not use if tamper evident seal is broken or missing. Store in a cool, dry place.

KEEP OUT OF REACH OF CHILDREN:

In case of overdose, get medical help or contact a Poison Control Center right away.

DIRECTIONS:

Adults and children 5 to 10 drops orally, 3 times daily or as otherwise directed by a health care professional. If symptoms persist for more than 7 days, consult your health care professional. Consult a physician for use in children under 12 years of age.

INDICATIONS:

May temporarily relieve symptoms associated with dairy sensitivities.**
**Claims based on traditional homeopathic practice, not accepted medical evidence. Not FDA evaluated.

INACTIVE INGREDIENTS:

Demineralized water, 20% Ethanol.

QUESTIONS:

Dist. by Energique, Inc.

201 Apple Blvd

Woodbine, IA 51579 800-869-8078

PACKAGE LABEL DISPLAY:

ENERGIQUE

SINCE 1987

HOMEOPATHIC REMEDY

DAIRY

ANTIGENS

1 fl. oz. (30 ml)